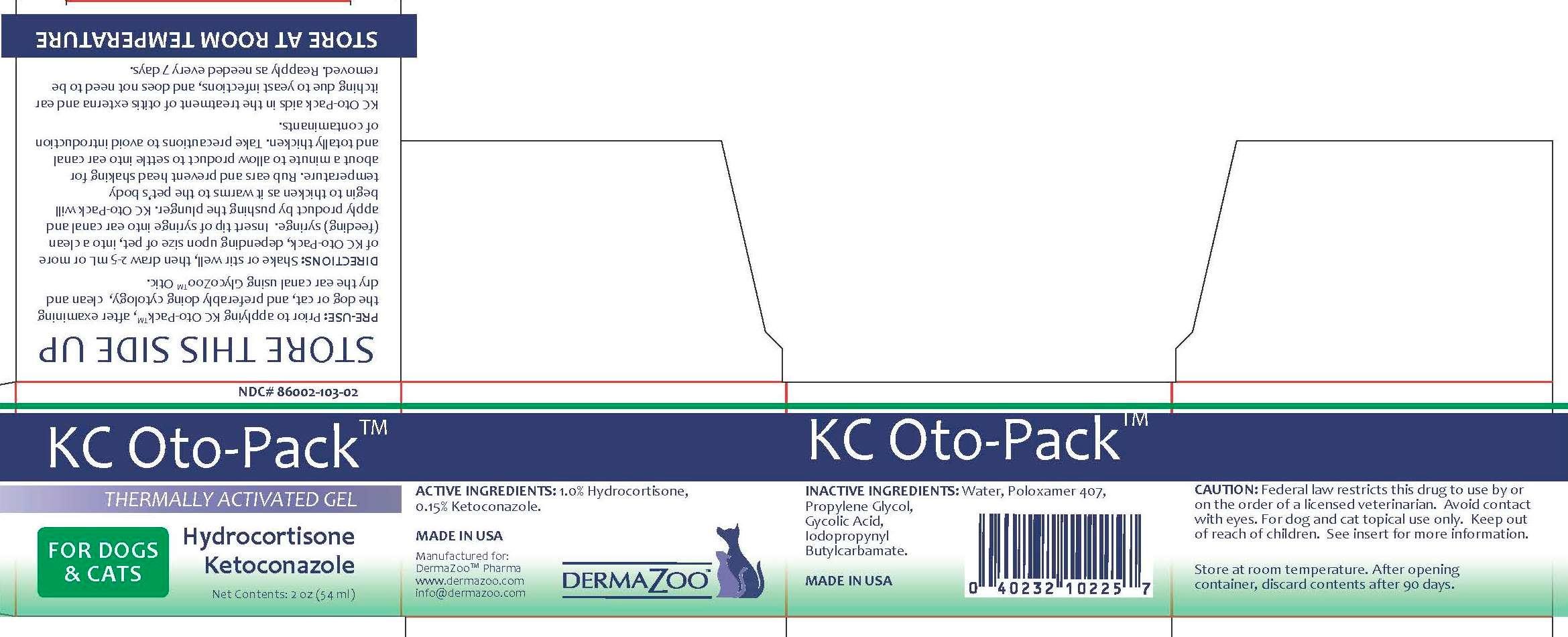 DRUG LABEL: KC Oto-Pack
NDC: 86002-103 | Form: GEL
Manufacturer: DermaZoo, LLC
Category: animal | Type: PRESCRIPTION ANIMAL DRUG LABEL
Date: 20150320

ACTIVE INGREDIENTS: HYDROCORTISONE 1 g/1000 mL; KETOCONAZOLE 0.15 g/1000 mL
INACTIVE INGREDIENTS: WATER; POLOXAMER 407; PROPYLENE GLYCOL; GLYCOLIC ACID; IODOPROPYNYL BUTYLCARBAMATE

INDICATIONS AND USAGE

PRE-USE: Prior to applying KC Oto-Pack™, after examining the dog or cat, and preferably doing cytology, clean and dry the ear canal using GlycoZoo™ Otic.

DIRECTIONS: Shake or stir well, then draw 2-5 mL or more of KC Oto-Pack, depending upon size of pet, into a clean (feeding) syringe. Insert tip of syringe into ear canal and apply product by pushing the plunger. KC Oto-Pack will begin to thicken as it warms to the pet’s body temperature. Rub ears and prevent head shaking for about a minute to allow product to settle into ear canal and totally thicken. Take precautions to avoid introduction of contaminants.

KC Oto-Pack aids in the treatment of otitis externa and ear itching due to yeast infections, and does not need to be removed. Reapply as needed every 7 days.

WARNINGS AND PRECAUTIONS

CAUTION: Federal law restricts this drug to use by or on the order of a licensed veterinarian. Avoid contact with eyes. For dog and cat topical use only. Keep out of reach of children. See insert for more information.

DESCRIPTION

ACTIVE INGREDIENTS: 1.0% Hydrocortisone, 0.15% Ketoconazole

INACTIVE INGREDIENTS: Water, Poloxamer 407, Propylene Glycol, Gycolic Acid, Iodopropynyl Butylcarbamate

STORAGE CONDITIONS

STORE THIS SIDE UP

STORE AT ROOM TEMPERATURE

After opening container, discard contents after 90 days.

KC Oto-Pack™

THERMALLY ACTIVATED GEL

Hydrocortisone

Ketoconazole

FOR DOGS & CATS

Net Contents: 2 oz. (54 ml)

Made in USA

Manufactured for: DermaZoo™ Pharma, www.dermazoo.com, info@dermazoo.com